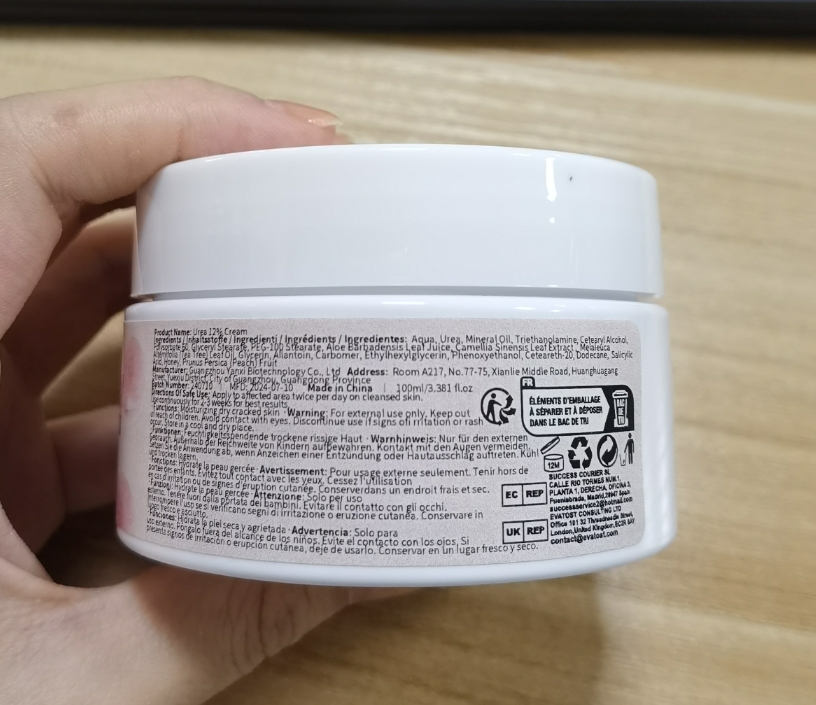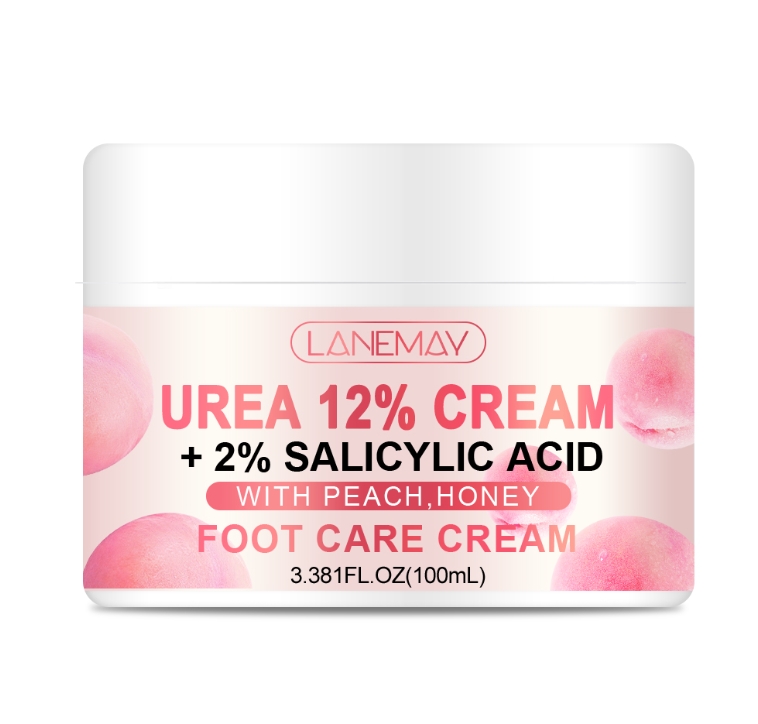 DRUG LABEL: Urea 12% Cream
NDC: 84025-091 | Form: CREAM
Manufacturer: Guangzhou Yanxi Biotechnology Co., Ltd
Category: otc | Type: HUMAN OTC DRUG LABEL
Date: 20240726

ACTIVE INGREDIENTS: MINERAL OIL 5 mg/100 mL; PEG-100 STEARATE 3 mg/100 mL
INACTIVE INGREDIENTS: WATER

DOSAGE AND ADMINISTRATION

use as a normal foot cream

WARNINGS

keep out of children

INACTIVE INGREDIENT

Aqua

INDICATIONS AND USAGE

for foot care

keep out of children

PURPOSE

moisturize feet